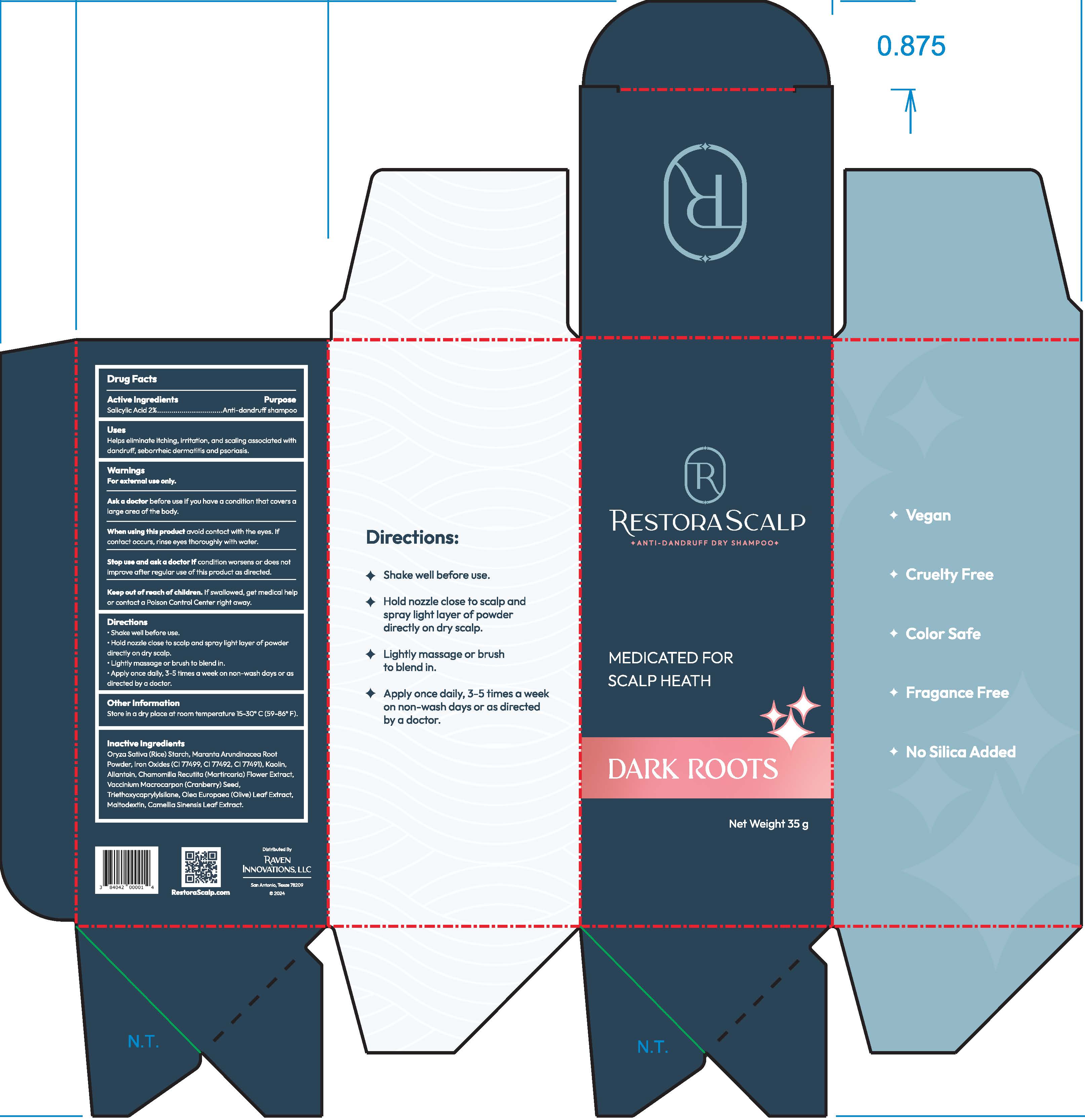 DRUG LABEL: RestoraScalp Anti Dandruff Dry Dark Roots
NDC: 84042-100 | Form: POWDER
Manufacturer: Raven Innovations LLC
Category: otc | Type: HUMAN OTC DRUG LABEL
Date: 20240710

ACTIVE INGREDIENTS: SALICYLIC ACID 2 g/100 g
INACTIVE INGREDIENTS: FERRIC OXIDE RED; KAOLIN; MARANTA ARUNDINACEA ROOT; STARCH, RICE; TRIETHOXYCAPRYLYLSILANE; CRANBERRY SEED; ALLANTOIN; FERRIC OXIDE YELLOW; MALTODEXTRIN; CHAMOMILE; OLEA EUROPAEA LEAF; GREEN TEA LEAF; FERROSOFERRIC OXIDE

Dark Roots

Active Ingredients

Salicylic Acid 2%

Purpose

Anti-dandruff shampoo

Uses

Helps eliminate itching, irritation, and scaling associated with dandruff, seborrheic dermatitis and psoriasis.

Warnings

For external use only.

Ask a doctor

before use if you have a condition that covers a large area of the body.

When using this product

avoid contact with the eyes. If contact occurs, rinse eyes thoroughly with water.

Stop use and ask a doctor

if condition worsens or does not improve after regular use of this product as directed.

Keep out of reach of children.

If swallowed, get medical help or contact a Poison Control Center right away.

Directions

Shake well before use
Hold nozzle close to scalp and spray light layer of powder directly on dry scalp
Lightly massage or brush to blend in
Apply once daily, 3-5 times a week on non-wash days or as directed by a doctor

Other Information

Store in a cool dry place at room temperature 15-30°C (59-86°F)

Inactive ingredients

Oryza Sativa (Rice) Starch, Maranta Arundinacea Root Powder, Iron Oxides (CI 77499, CI 77491, CI 77492), Kaolin, Allantoin, Chamomilla Recutita (Matricaria) Flower Extract, Vaccinium Macrocarpon (Cranberry) Seed, Triethoxycaprylylsilane, Olea Europaea (Olive) Leaf Extract, Maltodextrin, Camellia Sinensis Leaf Extract